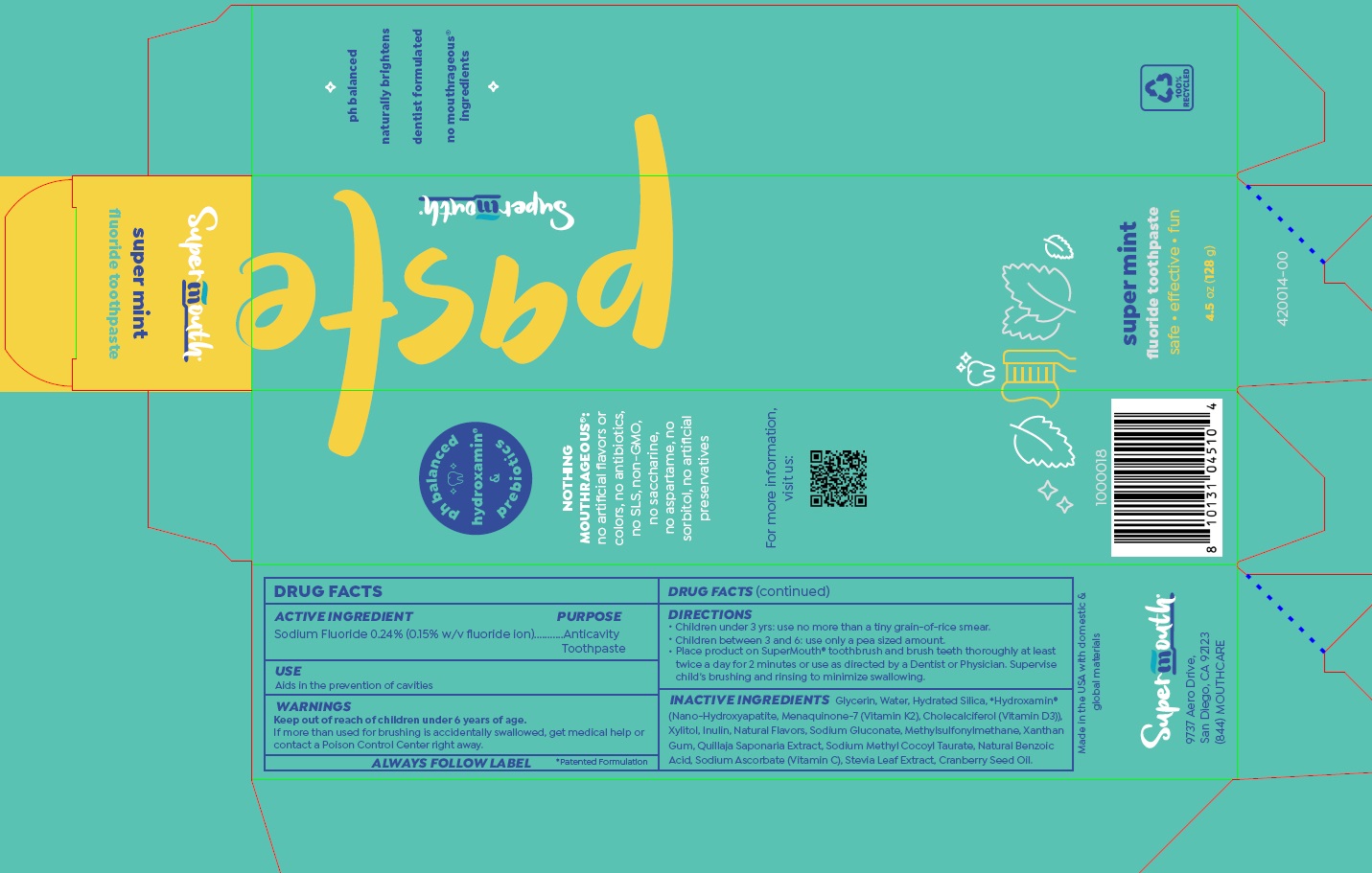 DRUG LABEL: Super Mint
NDC: 83729-121 | Form: PASTE, DENTIFRICE
Manufacturer: SuperMouth, LLC.
Category: otc | Type: HUMAN OTC DRUG LABEL
Date: 20251107

ACTIVE INGREDIENTS: SODIUM FLUORIDE 0.24 mg/100 g
INACTIVE INGREDIENTS: GLYCERIN; WATER; HYDRATED SILICA; TRIBASIC CALCIUM PHOSPHATE; MENAQUINONE 6; CHOLECALCIFEROL; XYLITOL; INULIN; SODIUM GLUCONATE; DIMETHYL SULFONE; XANTHAN GUM; QUILLAJA SAPONARIA ROOT; SODIUM METHYL COCOYL TAURATE; BENZOIC ACID; SODIUM ASCORBATE; STEVIA LEAF; CRANBERRY SEED OIL

Super Mint Toothpaste

DRUG FACTS

ACTIVE INGREDIENT

Sodium Fluoride 0.24% (0.15% w/v fluoride ion)

PURPOSE
Anticavity Toothpaste

USE

Aids in the prevention of cavities

WARNINGS

Keep out of reach of children under 6 years of age.

OTHER SAFETY INFORMATION

If more than used for brushing is accidentally swallowed, get medical help or
contact a Poison Control Center right away.

ALWAYS FOLLOW LABEL *patented formulation

DIRECTIONS

- Children under 3 yrs: use no more than a tiny grain-of-rice smear.

- Children between 3 and 6: use only a pea sized amount.

• Place product on SuperMouth® toothbrush and brush teeth thoroughly at least
twice a day for 2 minutes or use as directed by a Dentist or Physician. Supervise
child’s brushing and rinsing to minimize swallowing.

INACTIVE INGREDIENTS Glycerin, Water, Hydrated Silica, *Hydroxamin®
(Nano-Hydroxyapatite, Menaquinone-7 (Vitamin K2), Cholecalciferol (Vitamin D3)),
Xylitol, Inulin, Natural Flavors, Sodium Gluconate, Methylsulfonylmethane, Xanthan
Gum, Quillaja Saponaria Extract, Sodium Methyl Cocoyl Taurate, Natural Benzoic
Acid, Sodium Ascorbate (Vitamin C), Stevia Leaf Extract, Cranberry Seed Oil.

Product Labeling: Super Mint Flouride Toothpaste

..........................................................................

Supermouth

super mint

fluoride toothpaste

safe • effective • fun

4.5 oz (128 g)

SuperMouth®

9737 Aero Drive,
San Diego, CA 92123 U.S.A.
(844) MOUTHCARE

res